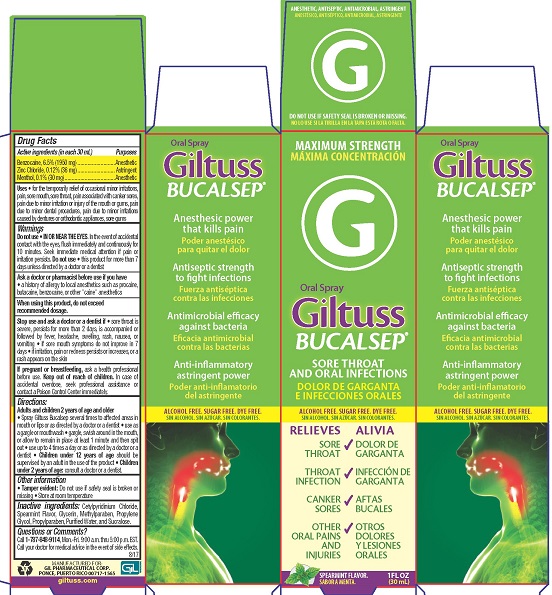 DRUG LABEL: Giltuss Bucalsep
NDC: 58552-135 | Form: SPRAY
Manufacturer: Gil Pharmaceutical Corp
Category: otc | Type: HUMAN OTC DRUG LABEL
Date: 20251009

ACTIVE INGREDIENTS: BENZOCAINE 6.5 g/100 mL; MENTHOL 0.1 g/100 mL; ZINC CHLORIDE 0.12 g/100 mL
INACTIVE INGREDIENTS: CETYLPYRIDINIUM CHLORIDE; SPEARMINT; GLYCERIN; METHYLPARABEN; PROPYLENE GLYCOL; PROPYLPARABEN; WATER; SUCRALOSE

Giltuss Bucalsep

Drug Facts

Active ingredients (in each 30 mL)

Benzocaine, 6.5% (1950 mg)

Zinc Chloride, 0.12% (36 mg)

Menthol, 0.1% (30 mg)

Purposes

Anesthetic

Astringent

Anesthetic

Warnings

Do not use

- IN OR NEAR THE EYES.In the event of accidental contact with the eyes, flush immediately and continuously for 10 minutes. Seek immediate medical attention if pain or irritation persists
- this product for more than 7 days unless directed by a doctor or a dentist

Ask a doctor or pharmacist before use if you have

- a history of allergy to local anesthetics such as procaine, butacaine, benzocaine, or other "caine" anesthetics

When using this product, do not exceed recommended dosage

Stop use and ask a doctor or dentist if

- sore throat is severe, persists for more than 2 days, is accompanied or followed by fever, headache, swelling, rash, nausea, or vomiting
- symptoms do not improve in 7 days
- irritation, pain or redness persists or increases, or a rash appears on the skin

PREGNANCY OR BREAST FEEDING

If pregnant or breast-feeding,ask a health professional before use.

Keep out of reach of children.In case of accidental overdose, seek professional assistance or contact a Poison Control Center immediately.

Directions

Adults and children 2 years of age and older:

- Spray Giltuss Bucalsep several times to affected areas in the mouth or lips or as directed by a doctor or dentist
- use as a gargle or mouthwash
- gargle, swish around in the mouth, or allow to remain in place at least 1 minute and then spit out
- use up to 4 times daily or as directed by a doctor or dentist
- Children under 12 years of age:should be supervised in the use of this product

Children under 2 years of age:consult a dentist or doctor

Other information

- Tamper evident:Do not use if safety seal is broken or missing
- Store at room temperature

Questions or Comments?

Call 1-800-848-9114, Mon. - Fri. 9:00 a.m. thru 5:00 p.m. EST. Call your doctor for medical advice in the event of side effects.

INACTIVE INGREDIENT

Inactive ingredients:Cetylpyridinium chloride, Spearmint Flavor, Glycerin, Methylparaben, Propylene Glycol, Propylparaben, Purified Water, Sucralose

MANUFACTURED FOR:

GIL PHARMACEUTICAL CORP.

PONCE, PUERTO RICO 00717-1565

giltuss.com

Uses

- for the temporary relief of occasional minor irritations, pain, sore mouth, sore throat, pain associated with canker sores, pain due to minor irritation or injury of the mouth and gums, pain due to dental procedures, pain due to minor irritations caused by dentures or orthodontic appliances, sore gums

PACKAGE LABEL

MAXIMUM STRENGTH

Oral Spray

Giltuss BUCALSEP®

SORE THROAT AND ORAL INFECTIONS

ALCOHOL FREE. SUGAR FREE. DYE FREE

RELIEVES

- SORE THROAT
- THROAT INFECTION
- CANKER SORES
- OTHER ORAL PAINS AND INJURIES

SPEARMINT FLAVOR

1FL OZ (30 mL)